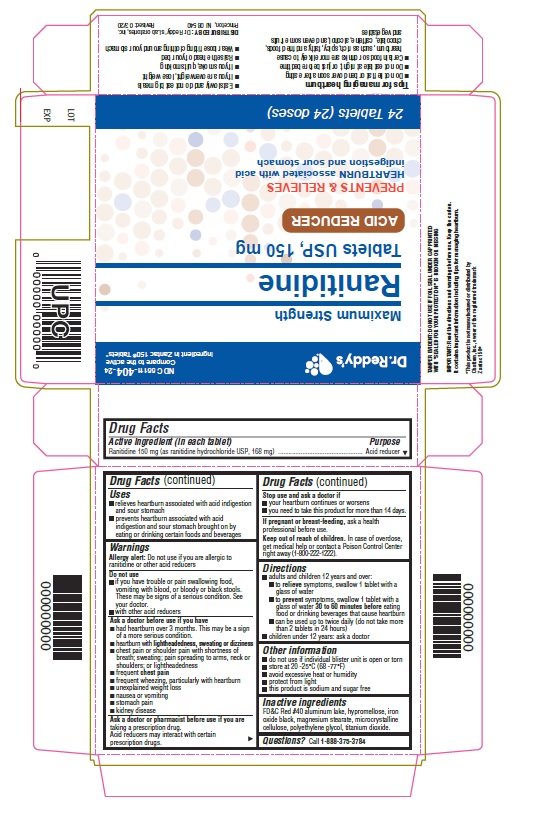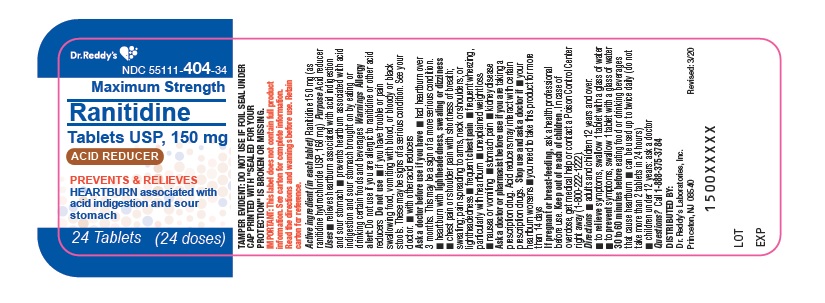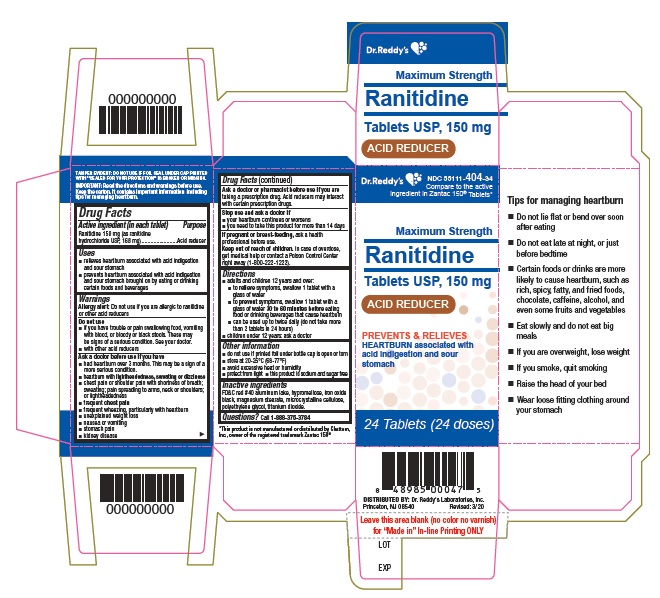 DRUG LABEL: Ranitidine
NDC: 55111-404 | Form: TABLET, COATED
Manufacturer: Dr. Reddy's Laboratories Limited
Category: otc | Type: HUMAN OTC DRUG LABEL
Date: 20250523

ACTIVE INGREDIENTS: Ranitidine Hydrochloride 150 mg/1 1
INACTIVE INGREDIENTS: FD&C RED NO. 40; HYPROMELLOSE 2910 (6 MPA.S); FERROSOFERRIC OXIDE; magnesium stearate; cellulose, microcrystalline; POLYETHYLENE GLYCOL 400; titanium dioxide

Drug Facts

Active ingredient (in each tablet)

Ranitidine 150 mg (as ranitidine hydrochloride USP, 168 mg)

Purpose

Acid reducer

Use(s)

- relieves heartburn associated with acid indigestion and sour stomach
- prevents heartburn associated with acid indigestion and sour stomach brought on by eating or drinking certain foods and beverages

Warnings

Allergy alert: Do not use if you are allergic to ranitidine or other acid reducers

Do not use

- if you have trouble or pain swallowing food, vomiting with blood, or bloody or black stools.These may be signs of a serious condition. See your doctor.
- with other acid reducers

Ask a doctor before use if you have

- had heartburn over 3 months. This may be a sign of a more serious condition.
- heartburn with lightheadedness, sweating or dizziness
- chest pain or shoulder pain with shortness of breath; sweating; pain spreading to arms, neck or shoulders; or lightheadedness
- frequent chest pain
- frequent wheezing, particularly with heartburn
- unexplained weight loss
- nausea or vomiting
- stomach pain
- kidney disease

Ask a doctor or pharmacist before use if you are

• taking a prescription drug. Acid reducers may interact with certain prescription drugs.

Stop use and ask doctor if

- your heartburn continues or worsens
- you need to take this product for more than 14 days

If pregnant or breast-feeding,

ask a health professional before use.

Keep out of reach of children.

In case of overdose, get medical help or contact a Poison Control Center right away (1-800-222-1222).

Directions

- adults and children 12 years and over:
  - to relieve symptoms, swallow 1 tablet with a glass of water
  - to prevent symptoms, swallow 1 tablet with a glass of water 30 to 60 minutes before eating food or drinking beverages that cause heartburn
  - can be used up to twice daily (do not take more than 2 tablets in 24 hours)
- children under 12 years: ask a doctor

Other information

- do not use if printed foil under bottle cap is open or torn
- store at 20°-25°C (68°-77°F)
- avoid excessive heat or humidity
- protect from light
- this product is sodium and sugar free

Inactive ingredients

FD&C red #40 aluminum lake, hypromellose, iron oxide black, magnesium stearate, microcrystalline cellulose, polyethylene glycol, titanium dioxide.

Questions?

Call 1-888-375-3784

Read the directions and warnings before use. Keep the carton. It contains important information including tips for managing heartburn.

Tips for managing heartburn

- Do not lie flat or bend over soon after eating
- Do not eat late at night, or just before bedtime
- Certain foods or drinks are more likely to cause heartburn, such as rich, spicy, fatty, and fried foods, chocolate, caffeine, alcohol, and even some fruits and vegetables.
- Eat slowly and do not eat beig meals
- If you are overweight, lose weight
- If you smoke, quit smoking
- Raise the head of your bed
- Wear loose fitting clothing around your stomach.

Revised: 03/20

PACKAGE LABEL PRINCIPAL DISPLAY PANEL

Container Label:

Dr.Reddy's
NDC 55111-404-34

Maximum Strength
Ranitidine
Tablets USP,150 mg
ACID REDUCER

PREVENTS & RELIEVES
HEARTBURN associated with acid indigestion
and sour stomach

24 Tablets(24 doses)

Container Carton Label:

Dr.Reddy's
NDC 55111-404-34

Compare to the active
ingredient in Zantact 150® Tablets*

Maximum Strength
Ranitidine
Tablets USP,150 mg
ACID REDUCER

PREVENTS & RELIEVES
heartburn associated with acid indigestion
and sour stomach

24 Tablets(24 doses)

Blister Carton Label:

Dr.Reddy's
NDC 55111-404-24

Maximum Strength
Ranitidine
Tablets USP,150 mg
ACID REDUCER

PREVENTS & RELIEVES
HEARTBURN associated with acid indigestion
and sour stomach

24 Tablets(24 doses)